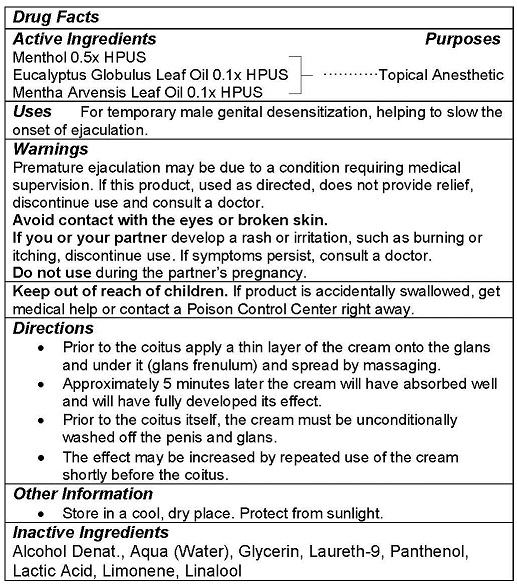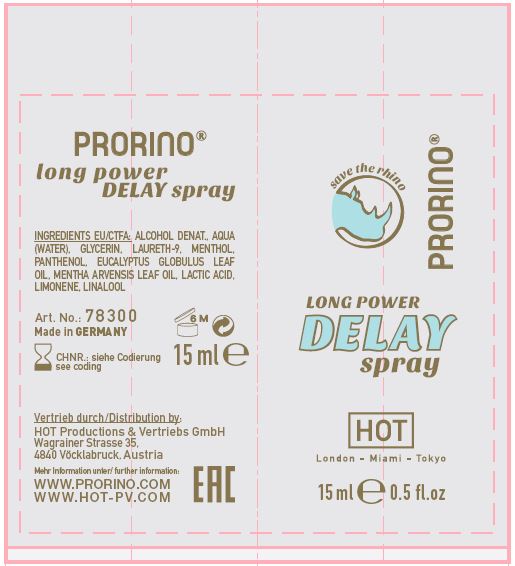 DRUG LABEL: PRORINO DELAY
NDC: 71326-202 | Form: SPRAY
Manufacturer: HOT PRODUCTIONS AND VERTRIEBS GMBH
Category: homeopathic | Type: HUMAN OTC DRUG LABEL
Date: 20231005

ACTIVE INGREDIENTS: MENTHOL 0.5 g/100 mL; EUCALYPTUS OIL 0.1 g/100 mL; MENTHA ARVENSIS LEAF OIL 0.1 g/100 mL
INACTIVE INGREDIENTS: ALCOHOL; WATER; GLYCERIN; POLIDOCANOL; PANTHENOL; LACTIC ACID; LIMONENE, (+)-; LINALOOL, (+)-

HOT PRODUCTS - Prorino Delay Spray (71326-202)

ACTIVE INGREDIENTS

Menthol 0.5x HPUS

Eucalyptus Globulus Leaf Oil 0.1x HPUS

Mentha Arvenes Leaf Oil 0.1x HPUS

PURPOSE

Topical Anesthetic

USE

For temporary male genital desensitization, helping to slow the onset of ejaculation.

WARNINGS

Premature ejaculation may be due to a condition requiring medical supervision. If this product, used as directed, does not provide relief, discontinue use and consult a doctor.
Avoid contact with the eyes or broken skin.
If you or your partner develop a rash or irritation, such as burning or itching, discontinue use. If symptoms persist, consult a doctor.
Do not use during the partner’s pregnancy.

Keep out of reach of children. If product is accidentally swallowed, get medical help or contact a Poison Control Center right away.

DIRECTIONS

- Prior to the coitus apply a thin layer of the cream onto the glans and under it (glans frenulum) and spread by massaging.
- Approximately 5 minutes later the cream will have absorbed well and will have fully developed its effect.
- Prior to the coitus itself, the cream must be unconditionally washed off the penis and glans.
- The effect may be increased by repeated use of the cream shortly before the coitus.

OTHER INFORMATION

- Store in a cool, dry place. Protect from sunlight.

INACTIVE INGREDIENTS

Alcohol Denat., Water (Aqua), Glycerin, Laureth-9, Panthenol, Lactic Acid, Limonene, Linalool